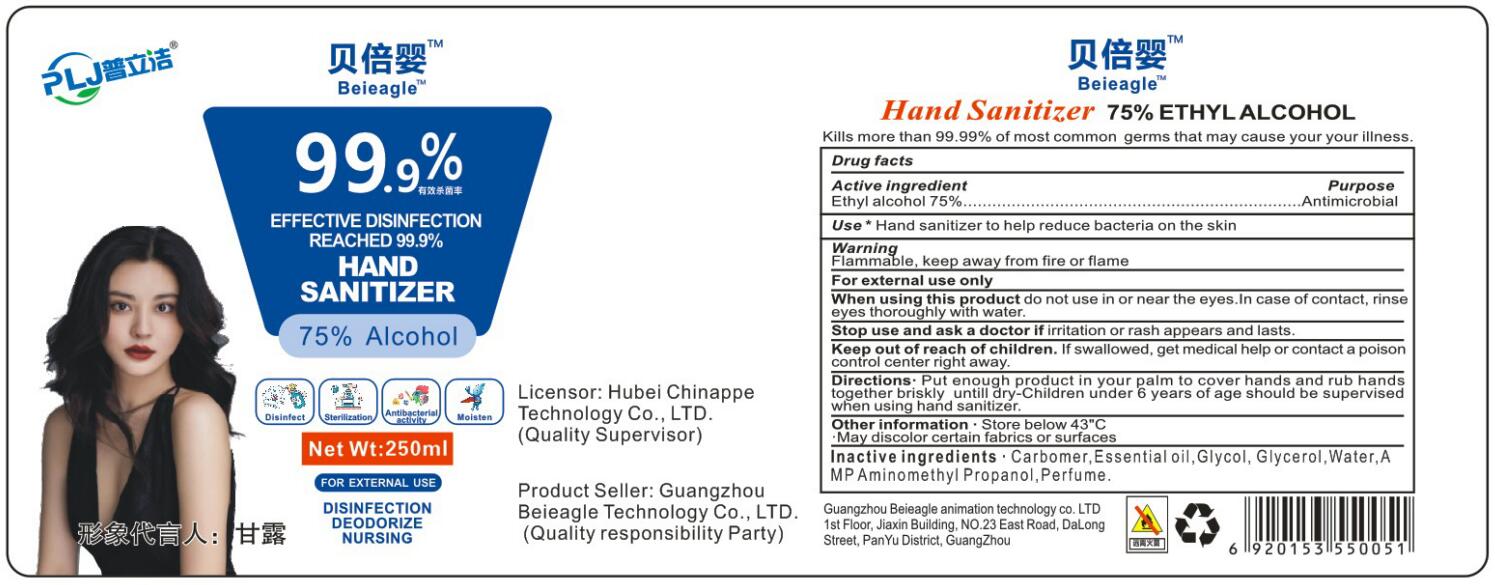 DRUG LABEL: HAND SANITIZER
NDC: 80720-001 | Form: GEL
Manufacturer: Guangzhou BEIEAGLE Technology Co. LTD
Category: otc | Type: HUMAN OTC DRUG LABEL
Date: 20201008

ACTIVE INGREDIENTS: ALCOHOL 75 mL/100 mL
INACTIVE INGREDIENTS: CARBOMER HOMOPOLYMER, UNSPECIFIED TYPE; ETHYLENE GLYCOL; LAVENDER OIL; GLYCERIN; FAGRAEA BERTEROANA FLOWER; WATER; AMINOMETHYLPROPANOL

80720-001
HAND SANITIZER

Active Ingredient(s)

Ethyl alcohol 75%

Purpose

Antimicrobial

Use

Hand sanitizer to help reduce bacteria on the skin

Warnings

FLAMMABLE.keep away from fire or flame.
For external use only

When using this product: do not use in or near the eyes.

In case of contact, rinse eyesthoughly with water.

Stop using this product If irritation or rash appears and

lasts

Keep out of reach of children If swallowed, get medical

help or contact a poison control center right away

Do not use

/

When using this product: do not use in or near the eyes. In case of contact, rinse eyesthoughly with water.

Stop using this product If irritation or rash appears and lasts

Keep out of reach of children If swallowed, get medical help or contact a poison control center right away

STOP USE

Stop using this product If irritation or rash appears and lasts

Keep out of reach of children If swallowed, get medical help or contact a poison control center right away

Directions

- Put enough product in your palm to cover hands and rub hands together briskly untill dry-children under 6 yeas of age should be supervised when using hand sanitizer

Other information

- Store below 43C
  May discotor certain fabrics or surfaces

Inactive ingredients

CARBOMER, ESSENTIAL OIL, GLYCOL, GLYCEROL, WATER, AMP AMINOMETHYL PROPANOL, PERFUME.